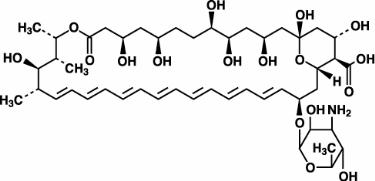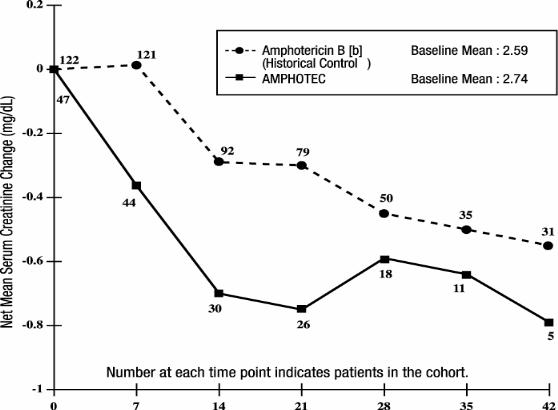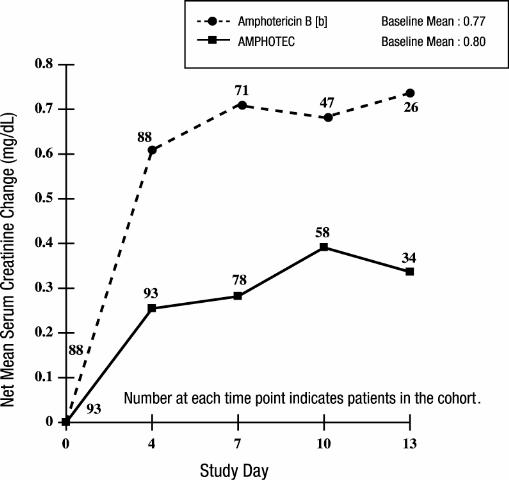 DRUG LABEL: Unknown
Manufacturer: InterMune, Inc.
Category: prescription | Type: Human Prescription Drug Label
Date: 20060227

AMPHOTEC®
Amphotericin B Cholesteryl Sulfate
Complex for Injection

DESCRIPTION

AMPHOTEC® is a sterile, pyrogen-free, lyophilized powder for reconstitution and intravenous (IV) administration. AMPHOTEC consists of a 1:1 (molar ratio) complex of amphotericin B and cholesteryl sulfate. Upon reconstitution, AMPHOTEC forms a colloidal dispersion of microscopic disc-shaped particles.

Note: Liposomal encapsulation or incorporation into a lipid complex can substantially affect a drug’s functional properties relative to those of the unencapsulated drug or non-lipid associated drug. In addition, different liposomal or lipid-complex products with a common active ingredient may vary from one another in the chemical composition and physical form of the lipid component. Such differences may affect the functional properties of these drug products.

Amphotericin B is an antifungal polyene antibiotic produced by a strain of Streptomyces nodosus.

Amphotericin B, which is the established name for [1R (1R*,3S*,5R*,6R*,9R*,11R*, 15S*,16R*,17R*,18S*,19E,21E,23E,25E,27E,29E,31E,33R*,35S*,36R*,37S*)]-33-[(3-Amino-3,6-dideoxy-ß-D-mannopyranosyl)oxy]-1,3,5,6,9,11,17,37-octahydroxy-15,16,18-trimethyl-13-oxo-14,39-dioxabicyclo[33.3.1] nonatriaconta-19,21,23,25,27, 29,31-heptaene-36-carboxylic acid, has the following structure:

The molecular formula of the drug is C47H73NO17; its molecular weight is 924.10.

AMPHOTEC is available in 50 mg and 100 mg single dose vials. Each 50 mg single dose vial contains amphotericin B, 50 mg; sodium cholesteryl sulfate, 26.4 mg; tromethamine, 5.64 mg; disodium edetate dihydrate, 0.372 mg; lactose monohydrate, 950 mg; and hydrochloric acid, qs, as a sterile, nonpyrogenic, lyophilized powder. Each 100 mg single dose vial contains amphotericin B, 100 mg; sodium cholesteryl sulfate, 52.8 mg; tromethamine, 11.28 mg; disodium edetate dihydrate, 0.744 mg; lactose monohydrate, 1900 mg; and hydrochloric acid, qs, as a sterile, nonpyrogenic, lyophilized powder.

MICROBIOLOGY

Mechanism of Action

The active ingredient of AMPHOTEC, amphotericin B, is a polyene antibiotic that acts by binding to sterols (primarily ergosterol) in cell membranes of sensitive fungi, with subsequent leakage of intracellular contents and cell death due to changes in membrane permeability. Amphotericin B also binds to the sterols (primarily cholesterol) in mammalian cell membranes, which is believed to account for its toxicity in animals and humans.

Activity in vitro and in vivo

AMPHOTEC is active in vitro against Aspergillus and Candida species. One hundred and twelve clinical isolates of four different Aspergillus species and 88 clinical isolates of five different Candida species were tested, with a majority of minimum inhibitory concentrations (MICs) < 1 μg/mL. AMPHOTEC is also active in vitro against other fungi. In vitro, AMPHOTEC is fungistatic or fungicidal, depending upon the concentration of the drug and the susceptibility of the fungal organism. However, standardized techniques for susceptibility testing for antifungal agents have not been established, and results of susceptibility studies do not necessarily correlate with clinical outcome.

AMPHOTEC is active in murine models against Aspergillus fumigatus, Candida albicans, Coccidioides immitis and Cryptococcus neoformans, and in an immunosuppressed rabbit model of aspergillosis in which endpoints were prolonged survival of infected animals and clearance of microorganisms from target organ(s). AMPHOTEC also was active in a hamster model of visceral leishmaniasis, a disease caused by infection of macrophages of the mononuclear phagocytic system by a protozoal parasite of the genus Leishmania. In this hamster model the endpoints were also prolonged survival of infected animals and clearance of microorganisms from target organ(s).

Drug Resistance

Variants with reduced susceptibility to amphotericin B have been isolated from several fungal species after serial passage in cell culture media containing the drug and from some patients receiving prolonged therapy with amphotericin B deoxycholate. Although the relevance of drug resistance to clinical outcome has not been established, fungal organisms that are resistant to amphotericin B may also be resistant to AMPHOTEC.

CLINICAL PHARMACOLOGY

Pharmacokinetics

The pharmacokinetics of amphotericin B, administered as AMPHOTEC, were studied in 51 bone marrow transplant patients with systemic fungal infections. The median (range) age and weight of those patients were 32 (3 to 52) years and 69.5 (14 to 116) kg, respectively. AMPHOTEC doses ranged from 0.5 to 8.0 mg/kg/day. The assay used in this study to measure amphotericin B in plasma does not distinguish amphotericin B that is complexed with cholesteryl sulfate from uncomplexed amphotericin B. A population modeling approach was used to estimate pharmacokinetic parameters (see table). The pharmacokinetics of amphotericin B, administered as AMPHOTEC, were best described by an open, two compartment structural model. The pharmacokinetics of amphotericin B, administered as AMPHOTEC, were nonlinear. Steady state volume of distribution (Vss) and total plasma clearance (CLt) increased with escalating doses, resulting in less than proportional increases in plasma concentration over a dose range of 0.5 to 8.0 mg/kg/day. The increased volume of distribution probably reflected uptake by tissues. The covariates of body weight and dose level accounted for a substantial portion of the variability of the pharmacokinetic estimates between patients. The unexplained variability in clearance was 26%. Based on the population model developed for these patients, pharmacokinetic parameters were predicted for two doses of AMPHOTEC and are provided in the following table:

Predicted Pharmacokinetic Parameters of Amphotericin B after Administration of Multiple Doses of AMPHOTEC [a]
 | AMPHOTEC (mg/kg/day)
Mean Pharmacokinetic Parameter [b] | 3 | 4
Vss (L/kg) | 3.8 | 4.1
CLt (L/h/kg) | 0.105 | 0.112
Distribution Half-Life (minutes) | 3.5 | 3.5
Elimination Half-Life (hours) | 27.5 | 28.2
Cmax (μg/mL) | 2.6 | 2.9
AUCss (μg/mL•h) | 29 | 36
[a] Data obtained using population modeling in 51 bone marrow transplant patients. The modeling assumes amphotericin B pharmacokinetics after administration of AMPHOTEC is best described by a 2-compartment model. Infusion rate = 1 mg/kg/hour.
[b] Definitions: Vss - Volume of distribution at steady state, CLt - Total plasma clearance, Cmax - Maximum plasma concentration achieved at the end of an infusion, AUCss – Area under the plasma concentration time curve at steady-state.

In addition, the pharmacokinetics of amphotericin B, administered as amphotericin B deoxycholate, were studied in 15 patients in whom amphotericin B deoxycholate was administered for the treatment of aspergillus infections or empirical therapy. The median (range) age and weight for these patients were 21 (4 to 66) years and 60 (19 to 117) kg, respectively. A population modeling approach was used to estimate the pharmacokinetic parameters. The pharmacokinetics of amphotericin B, administered as amphotericin B deoxycholate, was best described as an open, two-compartment model with linear elimination.

The predicted pharmacokinetic parameters are provided in the following table:

Predicted Pharmacokinetic Parameters of Amphotericin B after Administration of Multiple Doses of 1 mg/kg Amphotericin B Deoxycholate [a]
Mean Pharmacokinetic Parameter [b] | Values
Vss (L/kg) | 1.1
CLt (L/h/kg) | 0.028
Distribution Half-Life (minutes) | 38
Elimination Half-Life (hours) | 39
Cmax (μg/mL) | 2.9
AUCss (μg/mL•h) | 36
[a] Data obtained using population modeling in 15 patients in whom amphotericin B deoxycholate was administered for treatment of aspergillus infection or empiric therapy. The modeling assumes amphotericin B pharmacokinetics after administration of amphotericin B deoxycholate are best described by a 2-compartment model. Infusion rate = 0.25 mg/kg/hour.
[b] Definitions: Vss - Volume of distribution at steady state, CLt - Total plasma clearance, Cmax - Maximum plasma concentration achieved at the end of an infusion, AUCss - Area under the plasma concentration time curve at steady-state.

An analytical assay that is able to distinguish between amphotericin B in the AMPHOTEC complex and amphotericin B which is not complexed to cholesteryl sulfate was used to analyze samples from a study of 25 patients who were either immunocompromised with aspergillosis or both febrile and neutropenic. Following a 1 mg/kg/hour infusion, 25 ± 18% (mean ± SD) of the total amphotericin B concentration measured in plasma was in the AMPHOTEC complex, dropping to 9.3 ± 7.9% at 1 hour and 7.5 ± 9.3% at 24 hours after the end of the infusion.

Pharmacokinetics in Special Populations

A population modeling approach was used to assess the effect of renal function, hepatic function, and age on the pharmacokinetics of AMPHOTEC in 51 patients receiving bone marrow transplants as described earlier.

Renal Impairment: The pharmacokinetics of amphotericin B, administered as AMPHOTEC, were not related to baseline serum creatinine clearance in the population studied; the median (range) creatinine clearance for this population was 74.0 (range: 35 - 202) mL/min/70 kg. The effect of more severe renal impairment on the pharmacokinetics of AMPHOTEC has not been studied.

Hepatic Impairment: The pharmacokinetics of amphotericin B, administered as AMPHOTEC, were not related to baseline liver function, as determined by liver enzymes and total bilirubin. For the population tested, the mean ± SD values for AST and total Bilirubin were 59.4 ± 70.0 IU/mL and 3.5 ± 3.7 mg/dL, respectively. The effect of more severe hepatic impairment on the pharmacokinetics of AMPHOTEC has not been studied.

Age: The pharmacokinetics of amphotericin B, administered as AMPHOTEC, were not related to the age of the patient. The median (range) age for the population in this study was 32 (3 to 52) years.

INDICATIONS AND USAGE

AMPHOTEC is indicated for the treatment of invasive aspergillosis in patients where renal impairment or unacceptable toxicity precludes the use of amphotericin B deoxycholate in effective doses, and in patients with invasive aspergillosis where prior amphotericin B deoxycholate therapy has failed.

DESCRIPTION OF CLINICAL STUDIES

Clinical Studies in Aspergillosis

Data from 161 patients with proven or probable aspergillus infection were pooled from 5 non-comparative open label studies, one of which included emergency use patients. The patients were treated with AMPHOTEC because of failure to respond to amphotericin B deoxycholate (n=49), development of nephrotoxicity while receiving amphotericin B deoxycholate (n=62), preexisting renal impairment (n=25), or other reasons (n=25).

The median age of these 161 patients (92 males and 69 females) was 41 years (range 2 months to 85 years). For the 155 patients with baseline neutrophil data, 33 patients (21%) had neutrophil counts of < 500/mm3. The underlying diseases included bone marrow transplant, 69 (43%); hematological malignancy, 51(32%); solid organ transplant, 25 (15%); solid tumor, 3 (2%); and other diagnoses, 13 (8%) including surgery, 4; HIV infection, 3; immunosuppression for autoimmune disease, 3; diabetes, 2; and no known underlying disease, 1. Pulmonary involvement was the primary infection site, 118 patients (73%), followed by sinus, 14 (9%), CNS, 9 (6%), skin/wound, 9 (6%), and others, 10 (6%) including 3 with bone involvement, 2 with hepatic involvement, 2 with disseminated disease and 1 each with endocarditis, ophthalmitis, otitis, and involvement of the hard palate. The 49 patients enrolled due to failure to respond to amphotericin B had received amphotericin B deoxycholate prior to AMPHOTEC for ≤ 7 days (11 patients), 8 - 14 days (16 patients), and > 14 days (22 patients).

Patients were defined by their physicians as being refractory to amphotericin B deoxycholate therapy based on overall clinical judgment after receiving either a minimum of 7 days of amphotericin B deoxycholate or a minimum total dose of 15 mg/kg of amphotericin B deoxycholate. Nephrotoxicity was defined as a serum creatinine that had doubled from baseline, increased by ≥ 1.5 mg/dL or increased to ≥ 2.0 mg/dL. Preexisting renal impairment was defined as a serum creatinine that had increased to ≥ 2.0 mg/dL due to reasons other than amphotericin B deoxycholate administration.

Classifications of diagnosis and response were based on the definitions previously developed by the Mycoses Study Group.^1 A retrospective response analysis was conducted in which a “complete response” was defined as resolution of all attributable symptoms, signs, and radiographic abnormalities present at enrollment, and a “partial response” was defined as major improvement of the abovementioned parameters. The total number of responders was the sum of the number of “complete” and “partial” responses.

Of the 161 patients, 80 were considered evaluable for response. Eighty-one (81) were excluded on the basis of inadequate diagnosis, confounding factors, or receiving ≤ 4 doses of AMPHOTEC. In the evaluable patients, the median daily dose was 4 mg/kg/day (range 0.73 - 7.5 mg/kg/day) and the cumulative median dose was 6.3 g (range 0.36 - 34.4 grams). Median duration of treatment was 24 days (range 5 - 129 days).

Response Rates for Evaluable Patients
Patient Group (n) | Complete Response | Partial Response | Total Responders [a] | Response Rate
Amphotericin B deoxycholate failure (28) [b] | 3 | 9 | 12 | 43%
Nephrotoxicity (36) [c] | 5 | 12 | 17 | 47%
Preexisting renal impairment (16) [d] | 1 | 7 | 8 | 50%
Total (80) | 9 | 28 | 37 | 46%
[a] Total responders = Complete responses + Partial responses.
[b] Defined, based on overall clinical judgment, after receiving a minimum of 7 days of amphotericin B deoxycholate or a minimum total dose of 15 mg/kg of amphotericin B deoxycholate.
[c] Defined as a serum creatinine that had doubled from baseline or increased by ≥ 1.5 mg/dL or increased to ≥ 2.0 mg/dL.
[d] Defined as a serum creatinine that had increased to ≥ 2.0 mg/dL due to reasons other than amphotericin B deoxycholate.

There is no directly comparable control group for the patients described in the above table to be certain whether similar patients would have responded had amphotericin B deoxycholate therapy been continued. A randomized study comparing AMPHOTEC with amphotericin B deoxycholate for therapy of invasive aspergillosis is currently undergoing analysis.

Renal Function

Patients with Renal Dysfunction at Baseline

The subset of patients with aspergillosis from the above five noncomparative open label studies, who initiated treatment with AMPHOTEC when their serum creatinine was ≥ 2.0 mg/dL (n = 47) experienced a mean decline in serum creatinine during treatment. In part, this decline may be attributed to patient dropout over time from this group. A historical control group was selected by reviewing medical charts of patients from January 1990 to June 1994 at 6 medical centers (M.D. Anderson Cancer Center, Fred Hutchinson Cancer Research Center, H. Lee Moffitt Cancer Center, University of Pittsburgh, Memorial Sloan-Kettering Cancer Center, and Bone Marrow Transplant Program at Emory University). The mean change in serum creatinine was evaluated for similar cohorts of patients from this historical control group, with the baseline for assessing change being the day each patient’s serum creatinine reached ≥ 2.0 mg/dL. As shown in the figure, serum creatinine levels were lower during treatment with AMPHOTEC when compared to the serum creatinine levels of amphotericin B deoxycholate patients in the historical control group. There is no directly comparable group to be certain whether this decline is significantly better than the results of serum creatinine levels in patients who had continued on amphotericin B deoxycholate. Since these data were obtained from two separate studies, no statistical testing of the differences between these two groups was performed.

Changes in Mean Serum Creatinine Over Time in Patients with
Aspergillosis and Baseline Serum Creatinine ≥ 2.0 mg/dL [a]

[a] These curves do not represent the clinical course of a given patient, but that of an openlabel cohort of patients.

[b] Administered as amphotericin B deoxycholate.

Patients with Normal Renal Function at Baseline

In a randomized, double-blind, multicenter study, 213 febrile neutropenic patients were given empirically either 4 mg/kg/day of AMPHOTEC or 0.8 mg/kg/day of amphotericin B deoxycholate for a maximum of 14 days. This study was primarily designed to compare the safety profiles of these two treatments. NOTE: AMPHOTEC is NOT approved for empirical treatment in febrile neutropenic patients.

In the above study, patients had largely normal renal function at baseline; median serum creatinine levels were 0.8 mg/dL for both treatment groups. The mean change in serum creatinine was evaluated for patients with baseline creatinine ≤ 1.5 mg/dL. As shown in the graph, patients in both treatment groups showed an increase in serum creatinine while on study, however AMPHOTEC patients experienced significantly less creatinine increase at each time point.

Changes in Mean Serum Creatinine Over Time in Patients with Febrile
Neutropenia, and Baseline Serum Creatinine ≤ 1.5 mg/dL [a]

[a] These curves do not represent the clinical course of a given patient, but that of a cohort of patients.

[b] Administered as amphotericin B deoxycholate.

Hypokalemia

In the same empiric study, significantly more amphotericin B deoxycholate patients had at least one laboratory result of serum potassium < 3.0 mEq/L at least one time in the study compared with AMPHOTEC patients (23% vs. 7%), although concomitant supplemental potassium was allowed in the study design. Both groups received approximately equal amounts of potassium supplementation.

Hypomagnesemia

In the same empiric study, there was no overall trend for decreasing serum magnesium in either group.

CONTRAINDICATIONS

AMPHOTEC should not be administered to patients who have documented hypersensitivity to any of its components, unless, in the opinion of the physician, the advantages of using AMPHOTEC outweigh the risks of hypersensitivity.

WARNINGS

Anaphylaxis has been reported with amphotericin B deoxycholate and other amphotericin B-containing drugs. Immediate treatment of anaphylaxis or anaphylactoid reactions is required. Epinephrine, oxygen, intravenous steroids, and airway management should be administered as indicated. If severe respiratory distress occurs, the infusion should be immediately discontinued. The patient should not receive further infusions of AMPHOTEC.

PRECAUTIONS

General

AMPHOTEC should be administered intravenously. Acute infusionrelated reactions including fever, chills, hypoxia, hypotension, nausea, or tachypnea, may occur 1 to 3 hours after starting intravenous infusion. These reactions are usually more severe or more frequent with the initial doses of AMPHOTEC and usually diminish with subsequent doses. Acute infusion-related reactions can be managed by pretreatment with antihistamines and corticosteroids and/or by reducing the rate of infusion and by prompt administration of antihistamines and corticosteroids. (See ADVERSE REACTIONS).

Rapid intravenous infusion should be avoided.

Laboratory Tests

Particularly tests of renal and hepatic function, serum electrolytes, complete blood count and prothrombin time should be monitored as medically indicated.

Drug Interactions

No formal drug interaction studies have been conducted with AMPHOTEC®. When administered concomitantly, the following drugs are known to interact with amphotericin B; therefore the following drugs may interact with AMPHOTEC.

Antineoplastic Agents

Concurrent use of antineoplastic agents and amphotericin B may enhance the potential for renal toxicity, bronchospasm, and hypotension. Caution is urged when antineoplastic agents are given concomitantly with AMPHOTEC.

Corticosteroids and Corticotropin (ACTH)

Concurrent use of corticosteroids and corticotropin (ACTH) with amphotericin B may potentiate hypokalemia which could predispose the patient to cardiac dysfunction. If corticosteroids or corticotropin are used concomitantly with AMPHOTEC, serum electrolytes and cardiac function should be monitored.

Cyclosporine and Tacrolimus

In the same randomized, double-blind, empiric trial to compare AMPHOTEC and amphotericin B deoxycholate, patients with normal baseline serum creatinine were prospectively enrolled into four strata: adults receiving cyclosporine or tacrolimus (n=89); or pediatric patients (< 16 years old) receiving cyclosporine or tacrolimus (n=15); adults not receiving cyclosporine or tacrolimus (n=75); or pediatric patients not receiving cyclosporine or tacrolimus (n=34). Patients were assessed for renal toxicity defined as either a doubling or an increase of 1.0 mg/dL or more from baseline serum creatinine, or ≥ 50% decrease from baseline calculated creatinine clearance. Adults and pediatric patients receiving cyclosporine or tacrolimus in addition to AMPHOTEC had a significantly lower rate of renal toxicity (31%, 16/51), compared to the amphotericin B deoxycholate patients receiving cyclosporine or tacrolimus (68%, 34/50). In the adults and pediatric patients not receiving cyclosporine or tacrolimus, only 8% (4/51) of the AMPHOTEC patients experienced renal toxicity compared to 35% (17/49) of the amphotericin B deoxycholate patients.

Digitalis Glycosides

Concurrent use of amphotericin B may induce hypokalemia and may potentiate digitalis toxicity. If digitalis glycosides are administered concomitantly with AMPHOTEC, serum potassium levels should be closely monitored.

Flucytosine

Concurrent use of flucytosine with amphotericin B containing preparations may increase the toxicity of flucytosine by possibly increasing its cellular uptake and/or impairing its renal excretion. Caution is urged when flucytosine is given concomitantly with AMPHOTEC.

Imidazoles (e.g., ketoconazole, miconazole, clotrimazole, fluconazole, etc.)

Antagonism between amphotericin B and imidazole derivatives such as miconazole and ketoconazole which inhibit ergosterol synthesis, has been reported in both in vitro and in vivo animal studies. The clinical significance of these findings has not been determined.

Other Nephrotoxic Medications

Concurrent use of amphotericin B and agents such as aminoglycosides and pentamidine may enhance the potential for drug-induced renal toxicity. Caution is urged if aminoglycosides or pentamidine are used concomitantly with AMPHOTEC. Intensive monitoring of renal function is recommended in patients requiring any combination of nephrotoxic medications.

Skeletal Muscle Relaxants

Amphotericin B-induced hypokalemia may enhance the curariform effect of skeletal muscle relaxants (e.g., tubocurarine) due to hypokalemia. If skeletal muscle relaxants are administered concomitantly with AMPHOTEC, serum potassium levels should be closely monitored.

Carcinogenesis, Mutagenesis and Impairment of Fertility

No long-term studies in animals have been performed with AMPHOTEC or amphotericin B deoxycholate to evaluate carcinogenic potential. AMPHOTEC and/or amphotericin B deoxycholate were not mutagenic in vitro with and without an exogenous mammalian microsomal metabolic activation system when assayed in the Salmonella reverse mutation assay, the CHO chromosomal aberration assay and the mouse lymphoma forward mutation assay. AMPHOTEC was also negative in vivo in the mouse bone marrow micronucleus assay. No studies have been conducted to determine if AMPHOTEC affects fertility or if it produces adverse effects when administered peri- or post-natally in animals. In multiple dose toxicity studies of up to 13 weeks in rats at doses up to 0.5 times the recommended human dose and in dogs at doses up to 0.4 times the recommended human dose (based on body surface area), ovarian and testicular histology were unaffected.

Pregnancy

Teratogenic Effects. Pregnancy Category B:

There are no reports of pregnant women having been treated with AMPHOTEC. Reproductive studies with AMPHOTEC in rats at doses up to 0.4 times the recommended human dose and in rabbits at doses up to 1.1 times the recommended human dose have revealed no evidence of harm to the fetus due to treatment with AMPHOTEC. Because animal reproduction studies are not always predictive of human response and because adequate and well controlled studies have not been conducted in pregnant women, AMPHOTEC should be used during pregnancy only if the anticipated benefit to the patient outweighs the potential risk to the fetus.

Nursing Mothers

It is not known whether AMPHOTEC is excreted in milk. Because of the potential for serious adverse reactions in nursing infants from amphotericin B, a decision should be made to discontinue nursing or discontinue treatment with AMPHOTEC, taking into account the importance of the drug to the mother.

Pediatric Use

Ninety-seven pediatric patients with systemic fungal infections have been treated with AMPHOTEC, at daily doses (mg/kg) similar to those given to adults. No unexpected adverse events have been reported. In the same empiric, multicenter trial, pediatric patients (< 16 years) treated with AMPHOTEC had significantly less renal toxicity than amphotericin B deoxycholate patients. Only 12% (3/25) of pediatric patients treated with AMPHOTEC developed nephrotoxicity compared to 52% (11/21) of pediatric patients receiving amphotericin B deoxycholate. Renal toxicity defined as either a doubling or an increase of 1.0 mg/dL or more from baseline serum creatinine, or ≥ 50% decrease from baseline calculated creatinine clearance.

Geriatric Use

Sixty-eight patients at least 65 years of age have been treated with AMPHOTEC. No unexpected adverse events have been reported.

ADVERSE REACTIONS

The following adverse events are based on the experience of 572 AMPHOTEC patients from 5 open studies of patients with systemic fungal infections, of whom 526 were treated with a daily dose of 3 - 6 mg/kg. Additionally, comparative adverse event data from 150 AMPHOTEC (4 or 6 mg/kg/day) and 146 amphotericin B deoxycholate (0.8 or 1 mg/kg/day) patients in prospectively randomized doubleblinded studies of empiric treatment of febrile and neutropenic patients or treatment of aspergillosis are also provided.

Infusion-related adverse events: Infusion-related adverse events (1 to 3 hours after starting intravenous infusion) occurred most frequently in association with the first infusion of AMPHOTEC. Their frequency and severity decreased with subsequent dosing. Based on the combined non-comparative studies, 35% (197/569) of the patients reported chills or chills and fever, possibly or probably related to AMPHOTEC, on the first day of dosing, compared to 14% (58/422) by the seventh dose. In the comparative studies, a similar decreasing trend was noted for AMPHOTEC and amphotericin B deoxycholate.

Adverse events that were considered to be possibly or probably related to AMPHOTEC and that occurred in 5% or more of the patients are summarized in the table below:

Summary of Probably and Possibly Related Adverse Events Reported by ≥ 5% of AMPHOTEC Patients
 | Non-Comparative Studies |  | Comparative Studies [a]
Adverse Event | AMPHOTEC (n=572) % | AMPHOTEC Aspergillosis Patients (n=161) % | AMPHOTEC (n=150) % | Amphotericin B Deoxycholate (n=146) %
Body as a Whole
Chills | 50 | 55 | 77 | 56
Fever | 33 | 34 | 55 | 47
Headache | 5 | 8 | 4 | 3
Chills and fever | 3 | 3 | 7 | 2
Cardiovascular System
Hypotension | 10 | 9 | 12 | 5
Tachycardia | 10 | 12 | 9 | 5
Hypertension | 7 | 9 | 7 | 6
Digestive System
Nausea | 8 | 12 | 7 | 7
Nausea and vomiting | 7 | 11 | 4 | 7
Vomiting | 6 | 8 | 11 | 8
Liver function test abnormal | 4 | 4 | 11 | 8
Hemic and Lymphatic System
Thrombocytopenia | 6 | 7 | 1 | 1
Metabolic/Nutritional Disorders
Creatinine increased [b] | 12 | 12 | 21 | 34
Hypokalemia | 8 | 7 | 26 | 29
Hypomagnesemia | 4 | 7 | 6 | 11
Hyperbilirubinemia | 3 | 2 | 19 | 17
Alkaline phosphatase increased | 3 | 3 | 7 | 8
Hyperglycemia | 1 | 1 | 6 | 9
Respiratory System
Dyspnea | 5 | 4 | 9 | 4
Hypoxia | 5 | 6 | 9 | 5
[a] From AMPHOTEC (4 or 6 mg/kg/day) and amphotericin B deoxycholate (0.8 or 1 mg/kg/day) patients in prospectively randomized double-blinded studies of empiric treatment of febrile and neutropenic patients or treatment of first-line aspergillosis, respectively.
[b] Includes patients with “kidney function abnormal” which was associated with an increase in creatinine.

Additionally, the following adverse events also occurred in 5% or more of AMPHOTEC patients; however, the causal relationship of these adverse events is uncertain:

General (body as a whole)

Abdomen enlarged, abdominal pain, back pain, chest pain, face edema, injection site inflammation, mucous membrane disorder, pain, sepsis

Cardiovascular System

Cardiovascular disorder, hemorrhage, postural hypotension

Digestive System

Diarrhea, dry mouth, hematemesis, jaundice, stomatitis

Hemic and Lymphatic System

Anemia, coagulation disorder, prothrombin decreased

Metabolic and Nutritional Disorders

Edema, generalized edema, hypocalcemia, hypophosphatemia, peripheral edema, weight gain

Nervous System

Confusion, dizziness, insomnia, somnolence, thinking abnormal, tremor

Respiratory System

Apnea, asthma, cough increased, epistaxis, hyperventilation, lung disorder, rhinitis

Skin and Appendages

Maculopapular rash, pruritis, rash, sweating

Special Senses

Eye hemorrhage

Urogenital

Hematuria

The following adverse events occurred in 1% to less than 5% of AMPHOTEC patients. The causal association between these adverse events and AMPHOTEC is uncertain.

General (body as a whole)

Accidental injury, allergic reaction, asthenia, death, hypothermia, immune system disorder, infection, injection site pain, injection site reaction, neck pain

Cardiovascular System

Arrhythmia, atrial fibrillation, bradycardia, congestive heart failure, heart arrest, phlebitis, shock, supraventricular tachycardia, syncope, vasodilatation, venoocclusive liver disease, ventricular extrasystoles

Digestive System

Anorexia, bloody diarrhea, constipation, dyspepsia, fecal incontinence, gamma glutamyl transpeptidase increased, gastrointestinal disorder, gastrointestinal hemorrhage, gingivitis, glossitis, hepatic failure, melena, mouth ulceration, oral moniliasis, rectal disorder

Hemic and Lymphatic System

Ecchymosis, fibrinogen increased, hypochromic anemia, leukocytosis, leukopenia, petechia, thromboplastin decreased

Metabolic and Nutritional Disorders

Acidosis, BUN increased, dehydration, hyponatremia, hyperkalemia, hyperlipemia, hypernatremia, hypervolemia, hypoglycemia, hypoproteinemia, lactic dehydrogenase increased, AST (SGOT) increased, ALT (SGPT) increased, weight loss

Musculoskeletal System

Arthralgia, myalgia

Nervous System

Agitation, anxiety, convulsion, depression, hallucinations, hypertonia, nervousness, neuropathy, paresthesia, psychosis, speech disorder, stupor

Respiratory System

Hemoptysis, lung edema, pharyngitis, pleural effusion, respiratory disorder, sinusitis

Skin and Appendages

Acne, alopecia, petechial rash, skin discoloration, skin disorder, skin nodule, skin ulcer, urticaria, vesiculobullous rash

Special Senses

Amblyopia, deafness, ear disorder, tinnitus

Urogenital System

Albuminuria, dysuria, glycosuria, kidney failure, oliguria, urinary incontinence, urinary retention, urinary tract disorder

OVERDOSAGE

AMPHOTEC is not dialyzable. Amphotericin B deoxycholate overdose has been reported to result in cardio-respiratory arrest.

DOSAGE AND ADMINISTRATION

The recommended dose for adults and pediatric patients is 3 - 4 mg/kg as required, once a day.

AMPHOTEC, reconstituted in Sterile Water for Injection, is administered diluted in 5% Dextrose for Injection by intravenous infusion at a rate of 1 mg/kg/hour. A test dose immediately preceding the first dose is advisable when commencing all new courses of treatment. A small amount of drug (e.g., 10 mL of the final preparation containing between 1.6 to 8.3 mg) should be infused over 15 to 30 minutes and the patient carefully observed for the next 30 minutes.

The infusion time may be shortened to a minimum of 2 hours for patients who show no evidence of intolerance or infusion-related reactions. If the patient experiences acute reactions or cannot tolerate the infusion volume, the infusion time may be extended.

Directions for reconstitution and preparation of infusion admixture

AMPHOTEC must be reconstituted by addition of Sterile Water for Injection. Using sterile syringe and a 20-gauge needle, rapidly add the following volumes to the vial to provide a liquid containing 5 mg of amphotericin B per mL. Shake gently by hand, rotating the vial until all solids have dissolved. Note that the fluid may be opalescent or clear.

50 mg/vial | add | 10 mL Sterile Water for Injection
100 mg/vial | add | 20 mL Sterile Water for Injection

For infusion, further dilute the reconstituted liquid to a final concentration of approximately 0.6 mg/mL (range 0.16 mg/mL to 0.83 mg/mL). The following table provides dilution recommendations:

Dose of AMPHOTEC | Volume of Reconstituted AMPHOTEC | Infusion Bag Size for 5% Dextrose for Injection
10 – 35 mg | 2 – 7 mL | 50 mL
35 – 70 mg | 7 – 14 mL | 100 mL
70 – 175 mg | 14 – 35 mL | 250 mL
175 – 350 mg | 35 – 70 mL | 500 mL
350 – 1000 mg | 70 – 200 mL | 1000 mL

Do not reconstitute the lyophilized powder with saline or dextrose solutions, or admix the reconstituted liquid with saline or electrolytes.

The use of any solution other than those recommended, or the presence of a bacteriostatic agent (e.g., benzyl alcohol) in the solution may cause precipitation of AMPHOTEC. Do not filter or use an in-line filter with AMPHOTEC.

Do not mix the infusion admixture with other drugs. If administered through an existing intravenous line, flush with 5% Dextrose for Injection prior to, and following, infusion of AMPHOTEC, otherwise administer via a separate line.

Parenteral drug products should be inspected visually for particulate matter and discoloration prior to administration whenever solution and container permit. Do not use if a precipitate or foreign matter is present, or if the seal is not intact. Strict aseptic technique always should be observed during reconstitution and dilution since no preservatives are present in the lyophilized drug or in the solutions used for reconstitution and dilution.

After reconstitution, the drug should be refrigerated at 2-8°C (36-46°F) and used within 24 hours. Do not freeze. After further dilution with 5% Dextrose for Injection, the infusion should be stored in a refrigerator (2-8°C) and used within 24 hours. Partially used vials should be discarded.

HOW SUPPLIED

AMPHOTEC® (Amphotericin B) Cholesteryl Sulfate Complex for Injection is a sterile lyophilized powder supplied in single use glass vials. Each vial is individually packaged.

AMPHOTEC 50 mg in 20 mL vial (NDC 64116-025-01)

AMPHOTEC 100 mg in 50 mL vial (NDC 64116-021-01)

STORAGE

Store unopened vials of AMPHOTEC at 15-30°C (59-86°F).

AMPHOTEC should be retained in the carton until time of use.

Manufactured by:
Ben Venue Laboratories, Inc., Bedford, OH 44146, USA

Distributed by:
InterMune, Inc., Brisbane, CA 94005

U.S. Patent Numbers 4,822,777; 5,032,582; 5,194,266; 5,077,057.

Rx Only

REFERENCES

1 Denning DW, Lee JY, Hostetler JS, et al. NIAID Mycoses Study Group multicenter trial of oral itraconazole therapy for invasive aspergillosis.
Am J Med. 1994;97:135-144.

July 2001

LB-1004.2